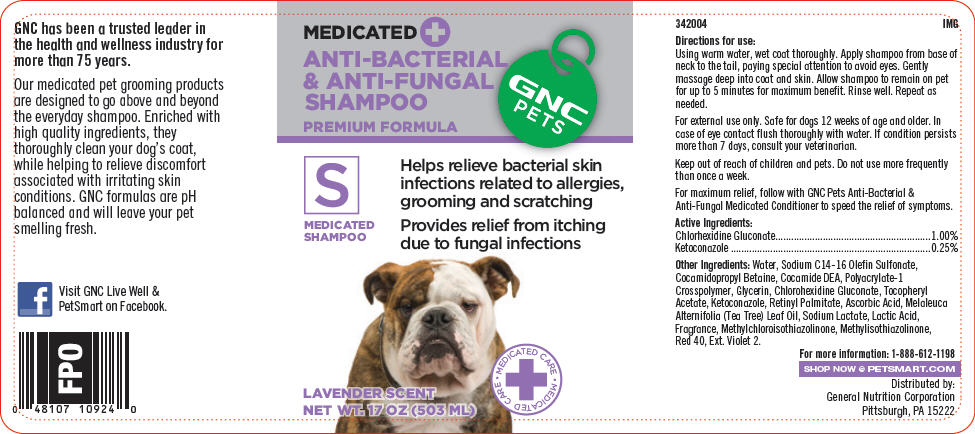 DRUG LABEL: GNC Pets Anti-Baceterial and Anti-Fungal (Premium Formula)
NDC: 43655-004 | Form: SHAMPOO
Manufacturer: General Nutrition Corporation
Category: animal | Type: OTC ANIMAL DRUG LABEL
Date: 20181105

ACTIVE INGREDIENTS: Chlorhexidine Gluconate 10 mg/1 mL; Ketoconazole 2.5 mg/1 mL
INACTIVE INGREDIENTS: Water; Sodium C14-16 Olefin Sulfonate; Cocamidopropyl Betaine; Coco Diethanolamide; Glycerin; .Alpha.-Tocopherol Acetate; Vitamin A Palmitate; Ascorbic Acid; Tea Tree Oil; Sodium Lactate; LACTIC ACID, UNSPECIFIED FORM; Methylchloroisothiazolinone; Methylisothiazolinone; FD&C RED NO. 40; EXT. D&C VIOLET NO. 2

GNC Pets Anti-Bacterial & Anti-Fungal Shampoo (Premium Formula)

342004
IMG

Directions for use:

Using warm water, wet coat thoroughly. Apply shampoo from base of neck to the tail, paying special attention to avoid eyes. Gently massage deep into coat and skin. Allow shampoo to remain on pet for up to 5 minutes for maximum benefit. Rinse well. Repeat as needed.

For external use only. Safe for dogs 12 weeks of age and older. In case of eye contact flush thoroughly with water. If condition persists more than 7 days, consult your veterinarian.

Keep out of reach of children and pets. Do not use more frequently than once a week.

For maximum relief, follow with GNC Pets Anti-Bacterial & Anti-Fungal Medicated Conditioner to speed the relief of symptoms.

Active Ingredients:

Chlorhexidine Gluconate | 1.00%
Ketoconazole | 0.25%

Other Ingredients: Water, Sodium C14-16 Olefin Sulfonate, Cocamidopropyl Betaine, Cocamide DEA, Polyacrylate-1 Crosspolymer, Glycerin, Chlorohexidine Gluconate, Tocopheryl Acetate, Ketoconazole, Retinyl Palmitate, Ascorbic Acid, Melaleuca Alternifolia (Tea Tree) Leaf Oil, Sodium Lactate, Lactic Acid, Fragrance, Methylchloroisothiazolinone, Methylisothiazolinone, Red 40, Ext. Violet 2.

For more information: 1-888-612-1198

SHOP NOW @ PETSMART.COM

Distributed by:
General Nutrition Corporation
Pittsburgh, PA 15222

PRINCIPAL DISPLAY PANEL - 503 ml Bottle Label

MEDICATED +
ANTI-BACTERIAL
& ANTI-FUNGAL
SHAMPOO

PREMIUM FORMULA

GNC
PETS

S
MEDICATED
SHAMPOO

Helps relieve bacterial skin
infections related to allergies,
grooming and scratching

Provides relief from itching
due to fungal infections

LAVENDER SCENT
NET WT. 17 OZ (503 ML)

• MEDICATED CARE •